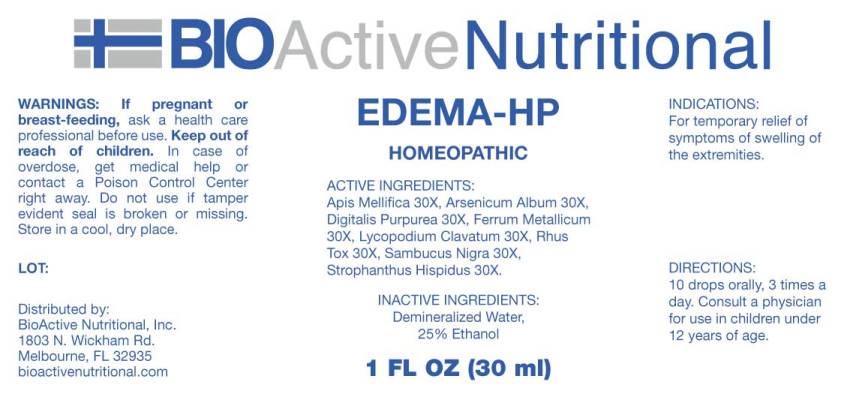 DRUG LABEL: Edema
NDC: 43857-0299 | Form: LIQUID
Manufacturer: BioActive Nutritional, Inc.
Category: homeopathic | Type: HUMAN OTC DRUG LABEL
Date: 20241017

ACTIVE INGREDIENTS: APIS MELLIFERA 30 [hp_X]/1 mL; ARSENIC TRIOXIDE 30 [hp_X]/1 mL; DIGITALIS 30 [hp_X]/1 mL; IRON 30 [hp_X]/1 mL; LYCOPODIUM CLAVATUM SPORE 30 [hp_X]/1 mL; TOXICODENDRON PUBESCENS LEAF 30 [hp_X]/1 mL; SAMBUCUS NIGRA FLOWERING TOP 30 [hp_X]/1 mL; STROPHANTHUS HISPIDUS SEED 30 [hp_X]/1 mL
INACTIVE INGREDIENTS: WATER; ALCOHOL

DRUG FACTS:

ACTIVE INGREDIENTS:

Apis Mellifica 30X, Arsenicum Album 30X, Digitalis Purpurea 30X, Ferrum Metallicum 30X, Lycopodium Clavatum 30X, Rhus Tox 30X, Sambucus Nigra 30X, Strophanthus Hispidus 30X.

INDICATIONS:

For temporary relief of symptoms of swelling of the extremities.

WARNINGS:

If pregnant or breast-feeding, ask a health care professional before use.

Keep out of reach of children. In case of overdose, get medical help or contact a Poison Control Center right away.

Do not use if tamper evident seal is broken or missing.

Store in a cool, dry place.

Keep out of reach of children. In case of overdose, get medical help or contact a Poison Control Center right away.

DIRECTIONS:

10 drops orally, 3 times a day. Consult a physician for use in children under 12 years of age.

INDICATIONS:

For temporary relief of symptoms of swelling of the extremities.

INACTIVE INGREDIENTS:

Demineralized Water, 25% Ethanol

QUESTIONS:

Distributed by:

BioActive Nutritional, Inc.

1803 N. Wickham Rd.

Melbourne, FL 32935

bioactivenutritional.com

PACKAGE LABEL DISPLAY:

BioActive Nutritional

EDEMA-HP

HOMEOPATHIC

1 FL OZ (30 ml)